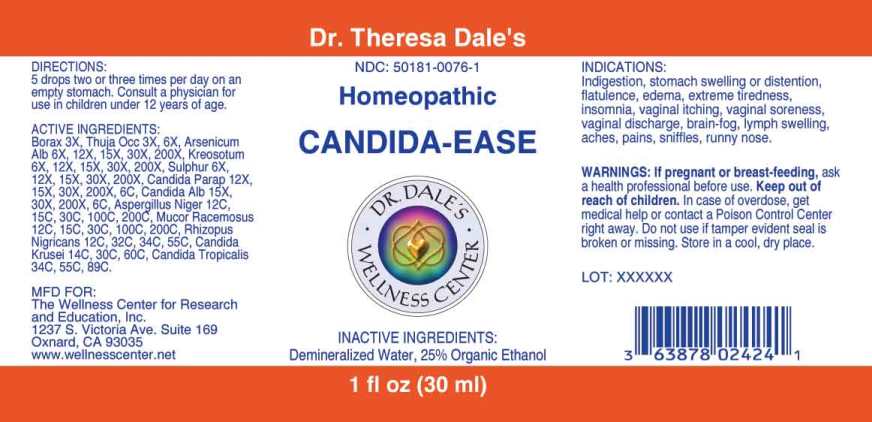 DRUG LABEL: Candida Ease
NDC: 50181-0076 | Form: LIQUID
Manufacturer: The Wellness Center for Research a
Category: homeopathic | Type: HUMAN OTC DRUG LABEL
Date: 20250606

ACTIVE INGREDIENTS: SODIUM BORATE 3 [hp_X]/1 mL; THUJA OCCIDENTALIS LEAFY TWIG 3 [hp_X]/1 mL; ARSENIC TRIOXIDE 6 [hp_X]/1 mL; WOOD CREOSOTE 6 [hp_X]/1 mL; SULFUR 6 [hp_X]/1 mL; CANDIDA PARAPSILOSIS 12 [hp_X]/1 mL; CANDIDA ALBICANS 15 [hp_X]/1 mL; ASPERGILLUS NIGER VAR. NIGER 12 [hp_C]/1 mL; MUCOR RACEMOSUS 12 [hp_C]/1 mL; RHIZOPUS STOLONIFER 12 [hp_C]/1 mL; ISSATCHENKIA ORIENTALIS WHOLE 14 [hp_C]/1 mL; CANDIDA TROPICALIS 34 [hp_C]/1 mL
INACTIVE INGREDIENTS: WATER; ALCOHOL

DRUG FACTS:

ACTIVE INGREDIENTS:

Borax 3X, Thuja Occidentalis 3X, 6X, Arsenicum Album 6X, 12X, 15X, 30X, 200X, Kreosotum 6X, 12X, 15X, 30X, 200X, Sulphur 6X, 12X, 15X, 30X, 200X, Candida Parapsilosis 12X, 15X, 30X, 200X, 6C, Candida Albicans 15X, 30X, 200X, 6C, Aspergillus Niger 12C, 15C, 30C, 100C, 200C, Mucor Racemosus 12C, 15C, 30C, 100C, 200C, Rhizopus Nigricans 12C, 32C, 34C, 55C, Candida Krusei 14C, 30C, 60C, Candida Tropicalis 34C, 55C, 89C.

INDICATIONS:

Indigestion, stomach swelling or distention, flatulence, edema, extreme tiredness, insomnia vaginal itching, vaginal soreness, vaginal discharge, brain-fog, lymph swelling, aches, pains, sniffles, runny nose.

WARNINGS:

If pregnant or breast-feeding, ask a health professional before use.

Keep out of reach of children. In case of overdose, get medical help or contact a Poison Control Center right away.

Do not use if tamper evident seal is broken or missing.

Store in a cool, dry place.

Keep out of reach of children. In case of overdose, get medical help or contact a Poison Control Center right away.

DIRECTIONS:

5 drops two or three times per day on an empty stomach. Consult a physician for use in children under 12 years of age.

INDICATIONS:

Indigestion, stomach swelling or distention, flatulence, edema, extreme tiredness, insomnia vaginal itching, vaginal soreness, vaginal discharge, brain-fog, lymph swelling, aches, pains, sniffles, runny nose.

INACTIVE INGREDIENTS:

Demineralized Water, 25% Organic Ethanol

QUESTONS:

MFD FOR:

The Wellness Center for

Research and Education, Inc.

1237 S. Victoria Ave, Suite 169

Oxnard, CA 93035

www.wellnesscenter.net

PACKAGE LABEL DISPLAY:

Dr. Theresa Dale's

NDC: 50181-0076-1

Homeopathic

CANDIDA-EASE

1 fl oz (30 ml)